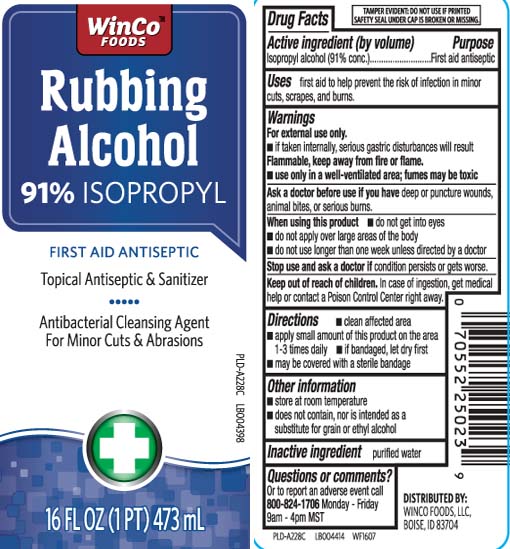 DRUG LABEL: Rubbing Alcohol
NDC: 67091-307 | Form: LIQUID
Manufacturer: WinCo Foods, LLC
Category: otc | Type: HUMAN OTC DRUG LABEL
Date: 20250212

ACTIVE INGREDIENTS: ISOPROPYL ALCOHOL 91 mL/100 mL
INACTIVE INGREDIENTS: WATER

Drug Facts

Active ingredient (by volume)

Isopropyl alcohol (91% conc.)

Purpose

first aid antiseptic

Uses

first aid to help prevent the risk of infection in minor cuts, scrapes and burns

Warnings

For external use only

- if taken internally, serious gastric disturbances will result

Flammable, keep away from fire or flame

- use only in a well-ventilated area;fumes may be toxic

Ask a doctor before use if you have

deep or puncture wounds, animal bites or serious burns

When using this product

- do not get into eyes
- do not apply over large areas of the body
- do not use longer than one week unless directed by a doctor

Stop use and ask a doctor if

condition persists or gets worse

Keep out of reach of children.

In case of ingestion, get medical help or contact a Poison Control Center (1-800-222-1222) immediately.

Directions

- clean affected area
- apply small amount of this product on the area 1-3 times daily
- if bandaged, let dry first
- may be covered with a sterile bandage

Other information

- store at room temperature
- does not contain, nor is intended as a substitute for grain or ethyl alcohol

Inactive ingredient

purified water

Questions or Comments?

Or to report an adverse event call 800-824-1706 Monday-Friday 9am-4pm MST

Principal Display Panel

Rubbing Alcohol

91% Isopropyl

FIRST AID ANTISEPTIC

Topical Antiseptic & Sanitizer

Antibacterial Cleansing Agent For Minor Cuts & Abrasions

fl oz (mL)

TAMPER EVIDENT: DO NOT USE IF PRINTED SAFETY FOIL UNDER CAP IS BROKEN OR MISSING

DISTRIBUTED BY:

WINCO FOODS, LLC

BOISE, ID 8370

Package Label

WINCO FOODS Rubbing Alcohol 91% Isopropyl